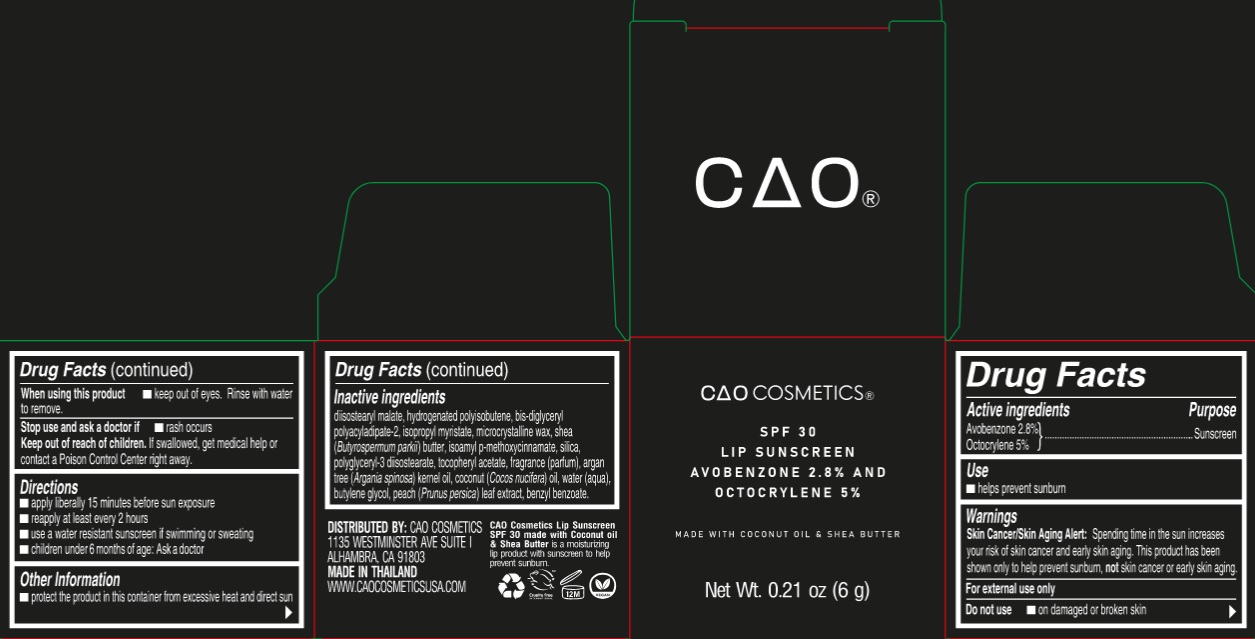 DRUG LABEL: CAO Cosmetic Lip Sunscreen SPF 30
NDC: 82564-000 | Form: OINTMENT
Manufacturer: S & J INTERNATIONAL ENTERPRISES PUBLIC COMPANY LIMITED
Category: otc | Type: HUMAN OTC DRUG LABEL
Date: 20231130

ACTIVE INGREDIENTS: AVOBENZONE 28 mg/1 g; OCTOCRYLENE 50 mg/1 g
INACTIVE INGREDIENTS: DIISOSTEARYL MALATE; BIS-DIGLYCERYL POLYACYLADIPATE-2; ISOPROPYL MYRISTATE; MICROCRYSTALLINE WAX; SHEA BUTTER; AMILOXATE; SILICON DIOXIDE; POLYGLYCERYL-3 DIISOSTEARATE; .ALPHA.-TOCOPHEROL ACETATE; COCONUT OIL; WATER; BUTYLENE GLYCOL; PRUNUS PERSICA LEAF; BENZYL BENZOATE

CAO Cosmetic Lip Sunscreen SPF 30

Active ingredients

Avobenzone 2.8%

Octocrylene 5%

Purpose

Sunscreen

Use

- helps prevent sunburn

Warnings

Spending time in the sun increases your risk of skin cancer and early skin aging. This product has been shown only to help prevent sunburn, not skin cancer or early skin aging. Skin Cancer/Skin Aging Alert: For external use only

Do not use

- on damaged or broken skin

When using this product

- keep out of eyes. Rinse with water to remove.

Stop use and ask a doctor if

- rash occurs

Keep out of reach of children.

If swallowed, get medical help or contact a Poison Control Center right away.

Directions

- apply liberally 15 minutes before sun exposure
- reapply at least every 2 hours
- use a water resistant sunscreen if swimming or sweating
- children under 6 months of age: Ask a doctor

Other Information

- protect the product in this container from excessive heat and direct sun

Inactive ingredients

diisostearyl malate, hydrogenated polyisobutene, bis-diglyceryl polyacyladipate-2, isopropyl myristate, microcrystalline wax, shea (Butyrospermum parkii) butter, isoamyl p-methoxycinnamate, silica, polyglyceryl-3 diisostearate, tocopheryl acetate, fragrance (parfum), argan tree (Argania spinosa) kernel oil, coconut (Cocos nucifera) oil, water (aqua), butylene glycol, peach (Prunus persica) leaf extract, benzyl benzoate.